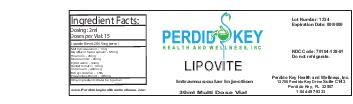 DRUG LABEL: Lipovite
NDC: 70104-128 | Form: INJECTION
Manufacturer: Perdido Key Health and Wellness Inc
Category: prescription | Type: HUMAN PRESCRIPTION DRUG LABEL
Date: 20151123

ACTIVE INGREDIENTS: LIDOCAINE 1 mg/1 mL; CITRULLINE 1 mg/1 mL; L-METHIONINE-S,R-SULFOXIMINE 1 mg/1 mL; CHOLINE 1 mg/1 mL; INOSITOL 1 mg/1 mL; THIAMINE 1 mg/1 mL; PYRIDOXINE 1 mg/1 mL; RIBOFLAVIN 1 mg/1 mL; NIACINAMIDE 1 mg/1 mL; METHYLCOBALAMIN 1 mg/1 mL; DEXPANTHENOL 1 mg/1 mL; CHROMIUM 1 mg/1 mL; LEVOCARNITINE 1 mg/1 mL

DOSAGE FORMS AND STRENGTHS

2ml